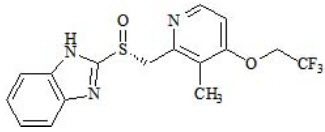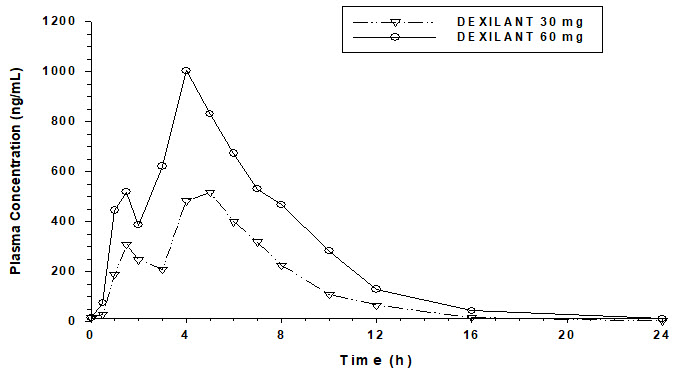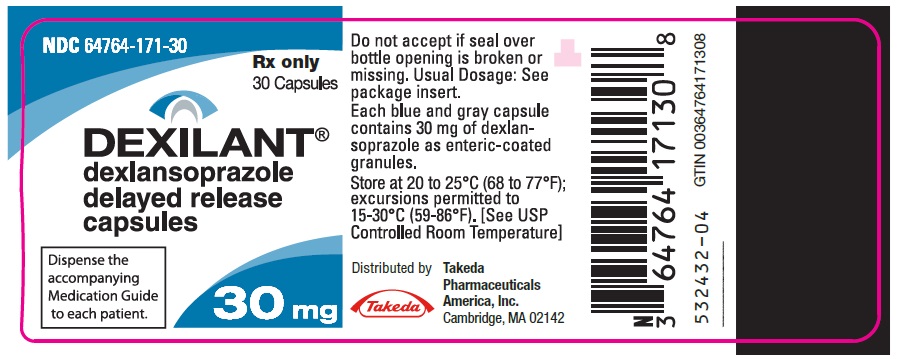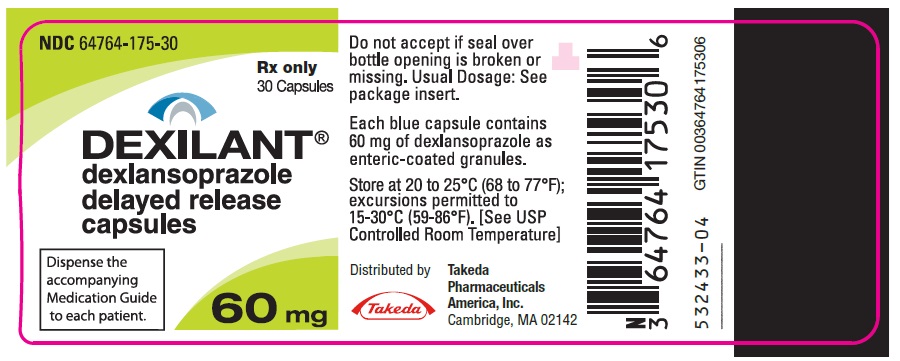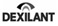 DRUG LABEL: Dexilant
NDC: 64764-171 | Form: CAPSULE, DELAYED RELEASE
Manufacturer: Takeda Pharmaceuticals America, Inc.
Category: prescription | Type: HUMAN PRESCRIPTION DRUG LABEL
Date: 20250217

ACTIVE INGREDIENTS: dexlansoprazole 30 mg/1 1
INACTIVE INGREDIENTS: Methacrylic Acid - Methyl Methacrylate Copolymer (1:1); Methacrylic Acid - Methyl Methacrylate Copolymer (1:2); METHACRYLIC ACID AND ETHYL ACRYLATE COPOLYMER; magnesium carbonate; sucrose; low-substituted hydroxypropyl cellulose, unspecified; titanium dioxide; HYDROXYPROPYL CELLULOSE (1600000 WAMW); HYPROMELLOSE 2910 (6 MPA.S); talc; polyethylene glycol 8000; triethyl citrate; polysorbate 80; silicon dioxide; carrageenan; potassium chloride; ferric oxide red; FD&C Blue No. 2; STARCH, CORN

HIGHLIGHTS OF PRESCRIBING INFORMATION

These highlights do not include all the information needed to use DEXILANT® safely and effectively. See full prescribing information for DEXILANT.
DEXILANT (dexlansoprazole) delayed-release capsules, for oral use
Initial U.S. Approval: 1995 (lansoprazole)

1 INDICATIONS AND USAGE

DEXILANT is a proton pump inhibitor (PPI) indicated in patients 12 years of age and older for:

- Healing of all grades of erosive esophagitis (EE). (1.1)
- Maintenance of healed EE and relief of heartburn. (1.2)
- Treatment of symptomatic non-erosive gastroesophageal reflux disease (GERD). (1.3)

2 DOSAGE AND ADMINISTRATION

Recommended dosage in patients 12 years of age and older:

- See full prescribing information for complete dosing information for DEXILANT by indication and age group and dosage adjustment in patients with hepatic impairment. (2.1, 2.2)

Administration Instructions (2.3):

- Take without regard to food.
- Swallow whole; do not chew.
- See full prescribing information for alternative administration options.

3 DOSAGE FORMS AND STRENGTHS

Delayed-release capsules: 30 mg and 60 mg. (3)

4 CONTRAINDICATIONS

- Patients with known hypersensitivity to any component of the formulation. (4)
- Patients receiving rilpivirine-containing products. (4, 7)

5 WARNINGS AND PRECAUTIONS

- Gastric Malignancy: In adults, symptomatic response with DEXILANT does not preclude the presence of gastric malignancy. Consider additional follow-up and diagnostic testing. (5.1)
- Acute Tubulointerstitial Nephritis: Discontinue treatment and evaluate patients. (5.2)
- Clostridium difficile-Associated Diarrhea: PPI therapy may be associated with increased risk. (5.3)
- Bone Fracture: Long-term and multiple daily dose PPI therapy may be associated with an increased risk for osteoporosis-related fractures of the hip, wrist or spine. (5.4)
- Severe Cutaneous Adverse Reactions: Discontinue at the first signs or symptoms of severe cutaneous adverse reactions or other signs of hypersensitivity and consider further evaluation. (5.5)
- Cutaneous and Systemic Lupus Erythematosus: Mostly cutaneous; new onset or exacerbation of existing disease; discontinue DEXILANT and refer to specialist for evaluation. (5.6)
- Cyanocobalamin (Vitamin B12) Deficiency: Daily long-term use (e.g., longer than 3 years) may lead to malabsorption or a deficiency of cyanocobalamin. (5.7)
- Hypomagnesemia and Mineral Metabolism: Reported rarely with prolonged treatment with PPIs. (5.8)
- Interactions with Investigations for Neuroendocrine Tumors: Increases in intragastric pH may result in hypergastrinemia and enterochromaffin-like cell hyperplasia and increased chromogranin A levels which may interfere with diagnostic investigations for neuroendocrine tumors. (5.9, 7)
- Interaction with Methotrexate: Concomitant use with PPIs may elevate and/or prolong serum concentrations of methotrexate and/or its metabolite, possibly leading to toxicity. With high-dose methotrexate administration, consider a temporary withdrawal of DEXILANT. (5.10, 7)
- Fundic Gland Polyps: Risk increases with long-term use, especially beyond 1 year. Use the shortest duration of therapy. (5.11)
- Risk of Heart Valve Thickening in Pediatric Patients Less than Two Years of Age: DEXILANT is not recommended in pediatric patients less than 2 years of age. (5.12, 8.4)

6 ADVERSE REACTIONS

The most common adverse reactions are:

- Adults (≥2%): diarrhea, abdominal pain, nausea, upper respiratory tract infection, vomiting, and flatulence. (6.1)
- Patients 12 to 17 years of age (≥5%): headache, abdominal pain, diarrhea, nasopharyngitis, and oropharyngeal pain. (6.1)

To report SUSPECTED ADVERSE REACTIONS, contact Takeda Pharmaceuticals America, Inc. at 1-877-TAKEDA-7 (1-877-825-3327) or FDA at 1-800-FDA-1088 or www.fda.gov/medwatch.

7 DRUG INTERACTIONS

See full prescribing information for a list of clinically important drug interactions. (7)

8 USE IN SPECIFIC POPULATIONS

- Pregnancy: Based on animal data, may cause adverse effects on fetal bone growth and development. (8.1)
- Pediatrics: Based on data with lansoprazole, DEXILANT is not effective in patients with symptomatic GERD 1 month to less than 1 year of age and nonclinical studies have demonstrated adverse effects in juvenile rats. (8.4)

FULL PRESCRIBING INFORMATION

1 INDICATIONS AND USAGE

1.1 Healing of Erosive Esophagitis

DEXILANT® is indicated in patients 12 years of age and older for healing of all grades of erosive esophagitis (EE) for up to eight weeks.

1.2 Maintenance of Healed Erosive Esophagitis and Relief of Heartburn

DEXILANT is indicated in patients 12 years of age and older to maintain healing of EE and relief of heartburn for up to six months in adults and 16 weeks in patients 12 to 17 years of age.

1.3 Treatment of Symptomatic Non-Erosive Gastroesophageal Reflux Disease

DEXILANT is indicated in patients 12 years of age and older for the treatment of heartburn associated with symptomatic non-erosive gastroesophageal reflux disease (GERD) for four weeks.

2 DOSAGE AND ADMINISTRATION

2.1 Recommended Dosage in Patients 12 Years of Age and Older

Table 1. Recommended DEXILANT Capsules Dosage Regimen by Indication in Patients 12 Years of Age and Older
Indication | Dosage of DEXILANT Capsules | Duration
Healing of EE | One 60 mg capsule once daily. | Up to 8 weeks.
Maintenance of Healed EE and Relief of Heartburn | One 30 mg capsule once daily. | Controlled studies did not extend beyond 6 months in adults and 16 weeks in patients 12 to 17 years of age.
Symptomatic Non-Erosive GERD | One 30 mg capsule once daily. | 4 weeks.

2.2 Dosage Adjustment in Patients with Hepatic Impairment for the Healing of Erosive Esophagitis

For patients with moderate hepatic impairment (Child-Pugh Class B), the recommended dosage is 30 mg DEXILANT once daily for up to eight weeks. DEXILANT is not recommended in patients with severe hepatic impairment (Child-Pugh Class C) [see Use in Specific Populations (8.6)].

2.3 Important Administration Information

- Take without regard to food.
- Missed doses: If a dose is missed, administer as soon as possible. However, if the next scheduled dose is due, do not take the missed dose, and take the next dose on time. Do not take two doses at one time to make up for a missed dose.
- Swallow whole; do not chew.
- For patients who have trouble swallowing capsules, DEXILANT capsules can be opened and administered with applesauce as follows:
  1. Place one tablespoonful of applesauce into a clean container.
  2. Open capsule.
  3. Sprinkle intact granules on applesauce.
  4. Swallow applesauce and granules immediately. Do not chew granules. Do not save the applesauce and granules for later use.
- Alternatively, the capsule can be administered with water via oral syringe or nasogastric (NG) tube.
  Administration with Water in an Oral Syringe
  1. Open the capsule and empty the granules into a clean container with 20 mL of water.
  2. Withdraw the entire mixture into a syringe.
  3. Gently swirl the syringe in order to keep granules from settling.
  4. Administer the mixture immediately into the mouth. Do not save the water and granule mixture for later use.
  5. Refill the syringe with 10 mL of water, swirl gently, and administer.
  6. Refill the syringe again with 10 mL of water, swirl gently, and administer.
  Administration with Water via a NG Tube (≥16 French)
  1. Open the capsule and empty the granules into a clean container with 20 mL of water.
  2. Withdraw the entire mixture into a catheter-tip syringe.
  3. Swirl the catheter-tip syringe gently in order to keep the granules from settling, and immediately inject the mixture through the NG tube into the stomach. Do not save the water and granule mixture for later use.
  4. Refill the catheter-tip syringe with 10 mL of water, swirl gently, and flush the tube.
  5. Refill the catheter-tip syringe again with 10 mL of water, swirl gently, and administer.

3 DOSAGE FORMS AND STRENGTHS

DEXILANT delayed-release capsules

- 30 mg: strength is an opaque, blue and gray capsule imprinted with "TAP" and "30".
- 60 mg: strength is an opaque, blue capsule imprinted with "TAP" and "60".

4 CONTRAINDICATIONS

- DEXILANT is contraindicated in patients with known hypersensitivity to any component of the formulation [see Description (11)]. Hypersensitivity reactions may include anaphylaxis, anaphylactic shock, angioedema, bronchospasm, acute tubulointerstitial nephritis and urticaria [see Warnings and Precautions (5.2), Adverse Reactions (6)].
- PPIs, including DEXILANT, are contraindicated with rilpivirine-containing products [see Drug Interactions (7)].

5 WARNINGS AND PRECAUTIONS

5.1 Presence of Gastric Malignancy

In adults, symptomatic response to therapy with DEXILANT does not preclude the presence of gastric malignancy. Consider additional follow-up and diagnostic testing in adult patients who have a suboptimal response or an early symptomatic relapse after completing treatment with a PPI. In older patients, also consider an endoscopy.

5.2 Acute Tubulointerstitial Nephritis

Acute tubulointerstitial nephritis (TIN) has been observed in patients taking PPIs and may occur at any point during PPI therapy. Patients may present with varying signs and symptoms from symptomatic hypersensitivity reactions to non-specific symptoms of decreased renal function (e.g., malaise, nausea, anorexia). In reported case series, some patients were diagnosed on biopsy and in the absence of extra-renal manifestations (e.g., fever, rash or arthralgia). Discontinue DEXILANT and evaluate patients with suspected acute TIN [see Contraindications (4)].

5.3 Clostridium difficile-Associated Diarrhea

Published observational studies suggest that PPI therapy like DEXILANT may be associated with an increased risk of Clostridium difficile-associated diarrhea, especially in hospitalized patients. This diagnosis should be considered for diarrhea that does not improve [see Adverse Reactions (6.2)].

Patients should use the lowest dose and shortest duration of PPI therapy appropriate to the condition being treated.

5.4 Bone Fracture

Several published observational studies suggest that PPI therapy may be associated with an increased risk for osteoporosis-related fractures of the hip, wrist or spine. The risk of fracture was increased in patients who received high-dose, defined as multiple daily doses, and long-term PPI therapy (a year or longer). Patients should use the lowest dose and shortest duration of PPI therapy appropriate to the conditions being treated. Patients at risk for osteoporosis-related fractures should be managed according to established treatment guidelines [see Dosage and Administration (2), Adverse Reactions (6.2)].

5.5 Severe Cutaneous Adverse Reactions

Severe cutaneous adverse reactions, including Stevens-Johnson syndrome (SJS) and toxic epidermal necrolysis (TEN), drug reaction with eosinophilia and systemic symptoms (DRESS), and acute generalized exanthematous pustulosis (AGEP) have been reported in association with the use of PPIs [see Adverse Reactions (6.2)]. Discontinue DEXILANT at the first signs or symptoms of severe cutaneous adverse reactions or other signs of hypersensitivity and consider further evaluation.

5.6 Cutaneous and Systemic Lupus Erythematosus

Cutaneous lupus erythematosus (CLE) and systemic lupus erythematosus (SLE) have been reported in patients taking PPIs. These events have occurred as both new onset and an exacerbation of existing autoimmune disease. The majority of PPI-induced lupus erythematosus cases were CLE.

The most common form of CLE reported in patients treated with PPIs was subacute CLE (SCLE) and occurred within weeks to years after continuous drug therapy in patients ranging from infants to the elderly. Generally, histological findings were observed without organ involvement.

Systemic lupus erythematosus (SLE) is less commonly reported than CLE in patients receiving PPIs. PPI-associated SLE is usually milder than nondrug induced SLE. Onset of SLE typically occurred within days to years after initiating treatment primarily in patients ranging from young adults to the elderly. The majority of patients presented with rash; however, arthralgia and cytopenia were also reported.

Avoid administration of PPIs for longer than medically indicated. If signs or symptoms consistent with CLE or SLE are noted in patients receiving DEXILANT, discontinue the drug and refer the patient to the appropriate specialist for evaluation. Most patients improve with discontinuation of the PPI alone in four to 12 weeks. Serological testing (e.g., ANA) may be positive and elevated serological test results may take longer to resolve than clinical manifestations.

5.7 Cyanocobalamin (Vitamin B12) Deficiency

Daily treatment with any acid-suppressing medications over a long period of time (e.g., longer than three years) may lead to malabsorption of cyanocobalamin (Vitamin B12) caused by hypo- or achlorhydria. Rare reports of cyanocobalamin deficiency occurring with acid-suppressing therapy have been reported in the literature. This diagnosis should be considered if clinical symptoms consistent with cyanocobalamin deficiency are observed in patients treated with DEXILANT.

5.8 Hypomagnesemia and Mineral Metabolism

Hypomagnesemia, symptomatic and asymptomatic, has been reported rarely in patients treated with PPIs for at least three months, in most cases after a year of therapy. Serious adverse events include tetany, arrhythmias, and seizures. Hypomagnesemia may lead to hypocalcemia and/or hypokalemia and may exacerbate underlying hypocalcemia in at-risk patients. In most patients, treatment of hypomagnesemia required magnesium replacement and discontinuation of the PPI.

For patients expected to be on prolonged treatment or who take PPIs with medications such as digoxin or drugs that may cause hypomagnesemia (e.g., diuretics), health care professionals may consider monitoring magnesium levels prior to initiation of PPI treatment and periodically [see Adverse Reactions (6.2)].

Consider monitoring magnesium and calcium levels prior to initiation of DEXILANT and periodically while on treatment in patients with a preexisting risk of hypocalcemia (e.g., hypoparathyroidism). Supplement with magnesium and/or calcium as necessary. If hypocalcemia is refractory to treatment, consider discontinuing the PPI.

5.9 Interactions with Investigations for Neuroendocrine Tumors

Serum chromogranin A (CgA) levels increase secondary to drug-induced decreases in gastric acidity. The increased CgA level may cause false positive results in diagnostic investigations for neuroendocrine tumors. Healthcare providers should temporarily stop dexlansoprazole treatment at least 14 days before assessing CgA levels and consider repeating the test if initial CgA levels are high. If serial tests are performed (e.g., for monitoring), the same commercial laboratory should be used for testing, as reference ranges between tests may vary [see Drug Interactions (7), Clinical Pharmacology (12.2)].

5.10 Interaction with Methotrexate

Literature suggests that concomitant use of PPIs with methotrexate (primarily at high dose) may elevate and prolong serum levels of methotrexate and/or its metabolite, possibly leading to methotrexate toxicities. In high- dose methotrexate administration, a temporary withdrawal of the PPI may be considered in some patients [see Drug Interactions (7)].

5.11 Fundic Gland Polyps

PPI use is associated with an increased risk of fundic gland polyps that increases with long-term use, especially beyond one year. Most PPI users who developed fundic gland polyps were asymptomatic and fundic gland polyps were identified incidentally on endoscopy. Use the shortest duration of PPI therapy appropriate to the condition being treated.

5.12 Risk of Heart Valve Thickening in Pediatric Patients Less Than Two Years of Age

DEXILANT is not recommended in pediatric patients less than two years of age. Nonclinical studies in juvenile rats with lansoprazole have demonstrated an adverse effect of heart valve thickening. Dexlansoprazole is the R-enantiomer of lansoprazole [see Use in Specific Populations (8.4)].

6 ADVERSE REACTIONS

The following serious adverse reactions are described below and elsewhere in labeling:

- Acute Tubulointerstitial Nephritis [see Warnings and Precautions (5.2)]
- Clostridium difficile-Associated Diarrhea [see Warnings and Precautions (5.3)]
- Bone Fracture [see Warnings and Precautions (5.4)]
- Severe Cutaneous Adverse Reactions [see Warnings and Precautions (5.5)]
- Cutaneous and Systemic Lupus Erythematosus [see Warnings and Precautions (5.6)]
- Cyanocobalamin (Vitamin B12) Deficiency [see Warnings and Precautions (5.7)]
- Hypomagnesemia and Mineral Metabolism [see Warnings and Precautions (5.8)]
- Fundic Gland Polyps [see Warnings and Precautions (5.11)]
- Risk of Heart Valve Thickening in Pediatric Patients Less than Two Years of Age [see Warnings and Precautions (5.12)]

6.1 Clinical Trials Experience

Because clinical trials are conducted under widely varying conditions, adverse reaction rates observed in the clinical trials of a drug cannot be directly compared to rates in the clinical trials of another drug and may not reflect the rates observed in practice.

Adults

The safety of DEXILANT was evaluated in 4,548 adult patients in controlled and single-arm clinical trials, including 863 patients treated for at least six months and 203 patients treated for one year. Patients ranged in age from 18 to 90 years (median age 48 years), with 54% female, 85% Caucasian, 8% Black, 4% Asian, and 3% Other races. Six randomized controlled clinical trials were conducted for the treatment of EE, maintenance of healed EE, and symptomatic GERD, which included 896 patients on placebo, 455 patients on DEXILANT 30 mg, 2,218 patients on DEXILANT 60 mg, and 1,363 patients on lansoprazole 30 mg once daily.

Common Adverse Reactions

The most common adverse reactions (≥2%) that occurred at a higher incidence for DEXILANT than placebo in the controlled studies are presented in Table 2.

Table 2. Common Adverse Reactions in Controlled Studies in Adults
Adverse Reaction | Placebo (N=896) % | DEXILANT 30 mg (N=455) % | DEXILANT 60 mg (N=2218) % | DEXILANT Total (N=2621) % | Lansoprazole 30 mg (N=1363) %
Diarrhea | 2.9 | 5.1 | 4.7 | 4.8 | 3.2
Abdominal Pain | 3.5 | 3.5 | 4.0 | 4.0 | 2.6
Nausea | 2.6 | 3.3 | 2.8 | 2.9 | 1.8
Upper Respiratory Tract Infection | 0.8 | 2.9 | 1.7 | 1.9 | 0.8
Vomiting | 0.8 | 2.2 | 1.4 | 1.6 | 1.1
Flatulence | 0.6 | 2.6 | 1.4 | 1.6 | 1.2

Adverse Reactions Resulting in Discontinuation

In controlled clinical studies, the most common adverse reaction leading to discontinuation from DEXILANT was diarrhea (0.7%).

Less Common Adverse Reactions

Other adverse reactions that were reported in controlled studies at an incidence of less than 2% are listed below by body system:

Blood and Lymphatic System Disorders: anemia, lymphadenopathy

Cardiac Disorders: angina, arrhythmia, bradycardia, chest pain, edema, myocardial infarction, palpitation, tachycardia

Ear and Labyrinth Disorders: ear pain, tinnitus, vertigo

Endocrine Disorders: goiter

Eye Disorders: eye irritation, eye swelling

Gastrointestinal Disorders: abdominal discomfort, abdominal tenderness, abnormal feces, anal discomfort, Barrett's esophagus, bezoar, bowel sounds abnormal, breath odor, colitis microscopic, colonic polyp, constipation, dry mouth, duodenitis, dyspepsia, dysphagia, enteritis, eructation, esophagitis, gastric polyp, gastritis, gastroenteritis, gastrointestinal disorders, gastrointestinal hypermotility disorders, GERD, GI ulcers and perforation, hematemesis, hematochezia, hemorrhoids, impaired gastric emptying, irritable bowel syndrome, mucus stools, oral mucosal blistering, painful defecation, proctitis, paresthesia oral, rectal hemorrhage, retching

General Disorders and Administration Site Conditions: adverse drug reaction, asthenia, chest pain, chills, feeling abnormal, inflammation, mucosal inflammation, nodule, pain, pyrexia

Hepatobiliary Disorders: biliary colic, cholelithiasis, hepatomegaly

Immune System Disorders: hypersensitivity

Infections and Infestations: candida infections, influenza, nasopharyngitis, oral herpes, pharyngitis, sinusitis, viral infection, vulvo-vaginal infection

Injury, Poisoning and Procedural Complications: falls, fractures, joint sprains, overdose, procedural pain, sunburn

Laboratory Investigations: ALP increased, ALT increased, AST increased, bilirubin decreased/increased, blood creatinine increased, blood gastrin increased, blood glucose increased, blood potassium increased, liver function test abnormal, platelet count decreased, total protein increased, weight increase

Metabolism and Nutrition Disorders: appetite changes, hypercalcemia, hypokalemia

Musculoskeletal and Connective Tissue Disorders: arthralgia, arthritis, muscle cramps, musculoskeletal pain, myalgia

Nervous System Disorders: altered taste, convulsion, dizziness, headaches, migraine, memory impairment, paresthesia, psychomotor hyperactivity, tremor, trigeminal neuralgia

Psychiatric Disorders: abnormal dreams, anxiety, depression, insomnia, libido changes

Renal and Urinary Disorders: dysuria, micturition urgency

Reproductive System and Breast Disorders: dysmenorrhea, dyspareunia, menorrhagia, menstrual disorder

Respiratory, Thoracic and Mediastinal Disorders: aspiration, asthma, bronchitis, cough, dyspnea, hiccups, hyperventilation, respiratory tract congestion, sore throat

Skin and Subcutaneous Tissue Disorders: acne, dermatitis, erythema, pruritus, rash, skin lesion, urticaria

Vascular Disorders: deep vein thrombosis, hot flush, hypertension

Additional adverse reactions that were reported in a long-term single-arm trial and were considered related to DEXILANT by the treating physician included: anaphylaxis, auditory hallucination, B-cell lymphoma, bursitis, central obesity, cholecystitis acute, dehydration, diabetes mellitus, dysphonia, epistaxis, folliculitis, gout, herpes zoster, hyperlipidemia, hypothyroidism, increased neutrophils, MCHC decrease, neutropenia, rectal tenesmus, restless legs syndrome, somnolence, tonsillitis.

Pediatrics

The safety of DEXILANT was evaluated in controlled and single-arm clinical trials including 166 pediatric patients, 12 to 17 years of age for the treatment of symptomatic non-erosive GERD, healing of EE, maintenance of healed EE and relief of heartburn [see Clinical Studies (14.4)].

The adverse reaction profile was similar to that of adults. The most common adverse reactions that occurred in ≥5% of patients were headache, abdominal pain, diarrhea, nasopharyngitis, and oropharyngeal pain.

Other Adverse Reactions

See the full prescribing information for lansoprazole for other adverse reactions not observed with DEXILANT.

6.2 Postmarketing Experience

The following adverse reactions have been identified during postapproval use of DEXILANT. Because these reactions are reported voluntarily from a population of uncertain size, it is not always possible to reliably estimate their frequency or establish a causal relationship to drug exposure.

Blood and Lymphatic System Disorders: autoimmune hemolytic anemia, idiopathic thrombocytopenic purpura

Ear and Labyrinth Disorders: deafness

Eye Disorders: blurred vision

Gastrointestinal Disorders: oral edema, pancreatitis, fundic gland polyps

General Disorders and Administration Site Conditions: facial edema

Hepatobiliary Disorders: drug-induced hepatitis

Immune System Disorders: anaphylactic shock (requiring emergency intervention), exfoliative dermatitis, SJS/TEN (some fatal), DRESS, AGEP, erythema multiforme

Infections and Infestations: Clostridium difficile-associated diarrhea

Metabolism and Nutrition Disorders: hypomagnesemia, hypocalcemia, hypokalemia, hyponatremia

Musculoskeletal System Disorders: bone fracture

Nervous System Disorders: cerebrovascular accident, transient ischemic attack

Renal and Genitourinary Disorders: acute renal failure, erectile dysfunction

Respiratory, Thoracic and Mediastinal Disorders: pharyngeal edema, throat tightness

Skin and Subcutaneous Tissue Disorders: generalized rash, leukocytoclastic vasculitis

7 DRUG INTERACTIONS

Tables 3 and 4 include drugs with clinically important drug interactions and interaction with diagnostics when administered concomitantly with DEXILANT and instructions for preventing or managing them.

Consult the labeling of concomitantly used drugs to obtain further information about interactions with PPIs.

Table 3. Clinically Relevant Interactions Affecting Drugs Coadministered with DEXILANT and Interactions with Diagnostics
Antiretrovirals
Clinical Impact: | The effect of PPIs on antiretroviral drugs is variable. The clinical importance and the mechanisms behind these interactions are not always known.; - Decreased exposure of some antiretroviral drugs (e.g., rilpivirine, atazanavir, and nelfinavir) when used concomitantly with dexlansoprazole may reduce antiviral effect and promote the development of drug resistance. - Increased exposure of other antiretroviral drugs (e.g., saquinavir) when used concomitantly with dexlansoprazole may increase toxicity of the antiretroviral drugs. - There are other antiretroviral drugs which do not result in clinically relevant interactions with dexlansoprazole.
Intervention: | Rilpivirine-containing products: Concomitant use with DEXILANT is contraindicated [see Contraindications (4)]. See prescribing information. Atazanavir: See prescribing information for atazanavir for dosing information. Nelfinavir: Avoid concomitant use with DEXILANT. See prescribing information for nelfinavir. Saquinavir: See the prescribing information for saquinavir and monitor for potential saquinavir toxicities. Other antiretrovirals: See prescribing information.
Warfarin
Clinical Impact: | Increased INR and prothrombin time in patients receiving PPIs and warfarin concomitantly. Increases in INR and prothrombin time may lead to abnormal bleeding and even death.
Intervention: | Monitor INR and prothrombin time. Dose adjustment of warfarin may be needed to maintain target INR range. See prescribing information for warfarin.
Methotrexate
Clinical Impact: | Concomitant use of PPIs with methotrexate (primarily at high dose) may elevate and prolong serum concentrations of methotrexate and/or its metabolite hydroxymethotrexate, possibly leading to methotrexate toxicities. No formal drug interaction studies of high-dose methotrexate with PPIs have been conducted [see Warnings and Precautions (5.10)].
Intervention: | A temporary withdrawal of DEXILANT may be considered in some patients receiving high-dose methotrexate.
Digoxin
Clinical Impact: | Potential for increased exposure of digoxin.
Intervention: | Monitor digoxin concentrations. Dose adjustment of digoxin may be needed to maintain therapeutic drug concentrations. See prescribing information for digoxin.
Drugs Dependent on Gastric pH for Absorption (e.g., iron salts, erlotinib, dasatinib, nilotinib, mycophenolate mofetil, ketoconazole/itraconazole)
Clinical Impact: | Dexlansoprazole can reduce the absorption of other drugs due to its effect on reducing intragastric acidity.
Intervention: | Mycophenolate mofetil (MMF): Coadministration of PPIs in healthy subjects and in transplant patients receiving MMF has been reported to reduce the exposure to the active metabolite, mycophenolic acid (MPA), possibly due to a decrease in MMF solubility at an increased gastric pH. The clinical relevance of reduced MPA exposure on organ rejection has not been established in transplant patients receiving DEXILANT and MMF. Use DEXILANT with caution in transplant patients receiving MMF. See the prescribing information for other drugs dependent on gastric pH for absorption.
Tacrolimus
Clinical Impact: | Potentially increased exposure of tacrolimus, especially in transplant patients who are intermediate or poor metabolizers of CYP2C19.
Intervention: | Monitor tacrolimus whole blood trough concentrations. Dose adjustment of tacrolimus may be needed to maintain therapeutic drug concentrations. See prescribing information for tacrolimus.
Interactions with Investigations of Neuroendocrine Tumors
Clinical Impact: | CgA levels increase secondary to PPI-induced decreases in gastric acidity. The increased CgA level may cause false positive results in diagnostic investigations for neuroendocrine tumors [see Warnings and Precautions (5.9), Clinical Pharmacology (12.2)].
Intervention: | Temporarily stop DEXILANT treatment at least 14 days before assessing CgA levels and consider repeating the test if initial CgA levels are high. If serial tests are performed (e.g., for monitoring), the same commercial laboratory should be used for testing, as reference ranges between tests may vary.
Interaction with Secretin Stimulation Test
Clinical Impact: | Hyper-response in gastrin secretion in response to secretin stimulation test, falsely suggesting gastrinoma.
Intervention: | Temporarily stop DEXILANT treatment at least 30 days before assessing to allow gastrin levels to return to baseline [see Clinical Pharmacology (12.2)].
False Positive Urine Tests for THC
Clinical Impact: | There have been reports of false positive urine screening tests for tetrahydrocannabinol (THC) in patients receiving PPIs.
Intervention: | An alternative confirmatory method should be considered to verify positive results.

Table 4. Clinically Relevant Interactions Affecting DEXILANT When Coadministered with Other Drugs and Substances
CYP2C19 or CYP3A4 Inducers
Clinical Impact: | Decreased exposure of dexlansoprazole when used concomitantly with strong inducers [see Clinical Pharmacology (12.3)].
Intervention: | St. John's Wort, rifampin: Avoid concomitant use with DEXILANT. Ritonavir-containing products: See prescribing information.
CYP2C19 or CYP3A4 Inhibitors
Clinical Impact: | Increased exposure of dexlansoprazole is expected when used concomitantly with strong inhibitors [see Clinical Pharmacology (12.3)].
Intervention: | Voriconazole: See prescribing information.

8 USE IN SPECIFIC POPULATIONS

8.1 Pregnancy

Risk Summary

There are no studies with dexlansoprazole use in pregnant women to inform a drug-associated risk. Dexlansoprazole is the R-enantiomer of lansoprazole, and published observational studies of lansoprazole use during pregnancy did not demonstrate an association of adverse pregnancy-related outcomes with lansoprazole (see Data).

In animal reproduction studies, oral administration of lansoprazole to rats during organogenesis through lactation at 1.8 times the maximum recommended human dexlansoprazole dose produced reductions in the offspring in femur weight, femur length, crown-rump length and growth plate thickness (males only) on postnatal Day 21 (see Data). These effects were associated with reduction in body weight gain. Advise pregnant women of the potential risk to the fetus.

The estimated background risk of major birth defects and miscarriage for the indicated population is unknown. All pregnancies have a background risk of birth defect, loss, or other adverse outcomes. In the US general population, the estimated background risk of major birth defects and miscarriage in clinically recognized pregnancies is 2 to 4% and 15 to 20%, respectively.

Data

Human Data

Dexlansoprazole is the R-enantiomer of lansoprazole. Available data from published observational studies failed to demonstrate an association of adverse pregnancy-related outcomes and lansoprazole use. Methodological limitations of these observational studies cannot definitely establish or exclude any drug- associated risk during pregnancy. In a prospective study by the European Network of Teratology Information Services, outcomes from a group of 62 pregnant women administered median daily doses of 30 mg of lansoprazole were compared to a control group of 868 pregnant women who did not take any PPIs. There was no difference in the rate of major malformations between women exposed to PPIs and the control group, corresponding to a Relative Risk (RR)=1.04, [95% Confidence Interval (CI) 0.25-4.21]. In a population-based retrospective cohort study covering all live births in Denmark from 1996 to 2008, there was no significant increase in major birth defects during analysis of first trimester exposure to lansoprazole in 794 live births. A meta-analysis that compared 1,530 pregnant women exposed to PPIs in at least the first trimester with 133,410 unexposed pregnant women showed no significant increases in risk for congenital malformations or spontaneous abortion with exposure to PPIs (for major malformations Odds Ratio (OR)=1.12, [95% CI 0.86- 1.45] and for spontaneous abortions OR=1.29, [95% CI 0.84-1.97]).

Animal Data

An embryo-fetal development study conducted in rabbits at oral dexlansoprazole doses up to 30 mg/kg/day (approximately nine times the maximum recommended human dexlansoprazole dose [60 mg/day] based on body surface area) during organogenesis showed no effects on fetuses due to dexlansoprazole. In addition, embryo-fetal development studies performed in rats with oral lansoprazole at doses up to 150 mg/kg/day (40 times the recommended human lansoprazole dose based on body surface area) during organogenesis and in rabbits with oral lansoprazole at doses up to 30 mg/kg/day (16 times the recommended human lansoprazole dose based on body surface area) during organogenesis revealed no effects on fetuses due to lansoprazole.

A pre- and postnatal developmental toxicity study in rats with additional endpoints to evaluate bone development was performed with lansoprazole at oral doses of 10 to 100 mg/kg/day (0.2 to 1.8 times the maximum recommended human dexlansoprazole dose of 60 mg based on dexlansoprazole AUC [area under the plasma concentration-time curve]) administered during organogenesis through lactation. Maternal effects observed at 100 mg/kg/day (1.8 times the maximum recommended human dexlansoprazole dose of 60 mg based on dexlansoprazole AUC) included increased gestation period, decreased body weight gain during gestation, and decreased food consumption. The number of stillbirths was increased at this dose, which may have been secondary to maternal toxicity. Body weight of pups was reduced at 100 mg/kg/day starting on postnatal Day 11. Femur weight, femur length, and crown-rump length were reduced at 100 mg/kg/day on postnatal Day 21. Femur weight was still decreased in the 100 mg/kg/day group at age 17 to 18 weeks. Growth plate thickness was decreased in the 100 mg/kg/day males on postnatal Day 21, and was increased in the 30 and 100 mg/kg/day males at age 17 to 18 weeks. The effects on bone parameters were associated with reduction in body weight gain.

8.2 Lactation

Risk Summary

There is no information regarding the presence of dexlansoprazole in human milk, the effects on the breastfed infant, or the effects on milk production. However, lansoprazole and its metabolites are present in rat milk. The developmental and health benefits of breastfeeding should be considered along with the mother's clinical need for DEXILANT and any potential adverse effects on the breastfed child from DEXILANT or from the underlying maternal condition.

8.4 Pediatric Use

The safety and effectiveness of DEXILANT have been established in pediatric patients 12 years to 17 years of age for the healing of all grades of EE, the maintenance of healed EE and relief of heartburn, and treatment of heartburn associated with symptomatic non-erosive GERD. Use of DEXILANT in this age group is supported by evidence from adequate and well-controlled studies of DEXILANT in adults with additional safety, efficacy and pharmacokinetic data in pediatric patients 12 to 17 years of age. The adverse reaction profile in patients 12 to 17 years of age was similar to adults [see Dosage and Administration (2.1), Adverse Reactions (6.1), Clinical Pharmacology (12.3), Clinical Studies (14)].

The safety and effectiveness of DEXILANT have not been established in pediatric patients less than 12 years of age.

DEXILANT is not recommended in pediatric patients less than two years of age [see Warnings and Precautions (5.12)]. Nonclinical studies in juvenile rats treated with lansoprazole (the racemic mixture) have demonstrated adverse effects of heart valve thickening and bone changes at dexlansoprazole exposures which are expected to be similar to or higher than the dexlansoprazole exposure in pediatric patients one year to two years of age, as described below in Juvenile Animal Toxicity Data.

The use of DEXILANT is not recommended for the treatment of symptomatic GERD in pediatric patients one month to less than one year of age because lansoprazole was not shown to be effective in a multicenter, double-blind controlled trial.

Juvenile Animal Toxicity Data

Heart Valve Thickening

In two oral toxicity studies, thickening of the mitral heart valve occurred in juvenile rats treated with lansoprazole. Heart valve thickening was observed primarily with oral dosing initiated on postnatal Day 7 (age equivalent to neonatal humans) and postnatal Day 14 (human age equivalent of approximately one year) at doses of 250 mg/kg/day and higher (at postnatal Day 7 and postnatal Day 14 respectively, 2.5 and 1.8 times the expected dexlansoprazole exposure based on AUC in pediatric patients one year to two years of age). The treatment durations associated with heart valve thickening ranged from 5 days to 8 weeks. The findings reversed or trended towards reversibility after a 4-week drug-free recovery period. The incidence of heart valve thickening after initiation of dosing on postnatal Day 21 (human age equivalent of approximately two years) was limited to a single rat (1/24) in groups given 500 mg/kg/day for 4 or 8 weeks (2.1 times the expected dexlansoprazole exposure based on AUC in pediatric patients one year to two years of age). Based on the low incidence of heart valve thickening in 21-day old rats and the equivalent human age, the risk of heart valve injury does not appear to be relevant to patients two years of age and older.

Bone Changes

In an eight-week oral toxicity study of lansoprazole in juvenile rats with dosing initiated on postnatal Day 7, doses equal to or greater than 100 mg/kg/day (dexlansoprazole exposure based on AUC approximately equal to that in pediatric patients one year to two years of age) produced delayed growth, with impairment of weight gain observed as early as postnatal Day 10 (age equivalent to neonatal humans). At the end of treatment, the signs of impaired growth at 100 mg/kg/day and higher included reductions in body weight (14 to 44% compared to controls), absolute weight of multiple organs, femur weight, femur length and crown-rump length. Femoral growth plate thickness was reduced only in males and only at the 500 mg/kg/day dose. The effects related to delayed growth persisted through the end of the four -week recovery period. Longer term data were not collected.

8.5 Geriatric Use

Of the total number of patients (n=4,548) in clinical studies of DEXILANT, 11% of patients were aged 65 years and over, while 2% were 75 years and over. No overall differences in safety or effectiveness were observed between these patients and younger patients and other reported clinical experience has not identified significant differences in responses between geriatric and younger patients, but greater sensitivity of some older individuals cannot be ruled out [see Clinical Pharmacology (12.3)].

8.6 Hepatic Impairment

No dosage adjustment for DEXILANT is necessary for patients with mild hepatic impairment (Child-Pugh Class A).

In a study of adult patients with moderate hepatic impairment (Child-Pugh Class B) who received a single dose of 60 mg DEXILANT, there was a significant increase in systemic exposure of dexlansoprazole compared to healthy subjects with normal hepatic function [see Clinical Pharmacology (12.3)]. Therefore, for patients with moderate hepatic impairment (Child-Pugh Class B), dosage reduction is recommended for the healing of EE [see Dosage and Administration (2.2)].

No studies have been conducted in patients with severe hepatic impairment (Child-Pugh Class C); the use of DEXILANT is not recommended for these patients [see Dosage and Administration (2.2)].

10 OVERDOSAGE

There have been no reports of significant overdose with DEXILANT. Multiple doses of DEXILANT 120 mg and a single dose of DEXILANT 300 mg did not result in death or other severe adverse events. However, serious adverse events of hypertension have been reported in association with twice daily doses of DEXILANT 60 mg. Nonserious adverse reactions observed with twice daily doses of DEXILANT 60 mg include hot flashes, contusion, oropharyngeal pain, and weight loss. Dexlansoprazole is not expected to be removed from the circulation by hemodialysis.

In the event of over-exposure, treatment should be symptomatic and supportive.

If over-exposure occurs, call your poison control center at 1-800-222-1222 for current information on the management of poisoning or over-exposure.

11 DESCRIPTION

The active ingredient in DEXILANT (dexlansoprazole) delayed-release capsules, a proton pump inhibitor, is (+)-2-[(R)-{[3-methyl-4-(2,2,2-trifluoroethoxy)pyridin-2-yl] methyl} sulfinyl]-1H-benzimidazole, a compound that inhibits gastric acid secretion. Dexlansoprazole is the R-enantiomer of lansoprazole (a racemic mixture of the R- and S-enantiomers). Its empirical formula is: C16H14F3N3O2S, with a molecular weight of 369.36.

Dexlansoprazole has the following chemical structure:

Dexlansoprazole is a white to nearly white crystalline powder which melts with decomposition at 140°C. Dexlansoprazole is freely soluble in dimethylformamide, methanol, dichloromethane, ethanol, and ethyl acetate; and soluble in acetonitrile; slightly soluble in ether; and very slightly soluble in water; and practically insoluble in hexane.

Dexlansoprazole is stable when exposed to light. Dexlansoprazole is more stable in neutral and alkaline conditions than acidic conditions.

Dexlansoprazole is supplied for oral administration as a dual delayed-release formulation in capsules. The capsules contain dexlansoprazole in a mixture of two types of enteric-coated granules with different pH-dependent dissolution profiles [see Clinical Pharmacology (12.3)].

DEXILANT delayed-release capsules are available in two dosage strengths: 30 and 60 mg, per capsule. Each capsule contains enteric-coated granules consisting of dexlansoprazole (active ingredient) and the following inactive ingredients: sugar spheres, magnesium carbonate, sucrose, low-substituted hydroxypropyl cellulose, titanium dioxide, hydroxypropyl cellulose, hypromellose 2910, talc, methacrylic acid copolymers, polyethylene glycol 8000, triethyl citrate, polysorbate 80, and colloidal silicon dioxide. The components of the capsule shell include the following inactive ingredients: hypromellose, carrageenan and potassium chloride. Based on the capsule shell color, blue contains FD&C Blue No. 2 (or FD&C Blue No. 2 aluminum lake); gray contains black ferric oxide; and both contain titanium dioxide.

12 CLINICAL PHARMACOLOGY

12.1 Mechanism of Action

Dexlansoprazole belongs to a class of antisecretory compounds, the substituted benzimidazoles, that suppress gastric acid secretion by specific inhibition of the (H^+, K^+)-ATPase at the secretory surface of the gastric parietal cell. Because this enzyme is regarded as the acid (proton) pump within the parietal cell, dexlansoprazole has been characterized as a gastric proton-pump inhibitor, in that it blocks the final step of acid production.

12.2 Pharmacodynamics

Antisecretory Activity

The effects of DEXILANT 60 mg (n=20) or lansoprazole 30 mg (n=23) once daily for five days on 24 hour intragastric pH were assessed in healthy subjects in a multiple-dose crossover study. The results are summarized in Table 5.

Table 5. Effect on 24 Hour Intragastric pH on Day 5 After Administration of DEXILANT or Lansoprazole
DEXILANT 60 mg | Lansoprazole 30 mg
Mean Intragastric pH
4.55 | 4.13
% Time Intragastric pH >4 (hours)
71 (17 hours) | 60 (14 hours)

Serum Gastrin Effects

The effect of dexlansoprazole on serum gastrin concentrations was evaluated in approximately 3,460 patients in clinical trials up to eight weeks and in 1,023 patients for up to six to 12 months. The mean fasting gastrin concentrations increased from baseline during treatment with 30 and 60 mg DEXILANT. In patients treated for more than six months, mean serum gastrin levels increased during approximately the first three months of treatment and were stable for the remainder of treatment. Mean serum gastrin levels returned to pretreatment levels within one month of discontinuation of treatment.

Increased gastrin causes enterochromaffin-like cell hyperplasia and increased serum CgA levels. The increased CgA levels may cause false positive results in diagnostic investigations for neuroendocrine tumors [see Warnings and Precautions (5.9)].

Enterochromaffin-Like Cell (ECL) Effects

There were no reports of ECL cell hyperplasia in gastric biopsy specimens obtained from 653 patients treated with DEXILANT 30, 60, or 90 mg for up to 12 months.

During lifetime exposure of rats dosed daily with up to 150 mg/kg/day of lansoprazole, marked hypergastrinemia was observed followed by ECL cell proliferation and formation of carcinoid tumors, especially in female rats [see Nonclinical Toxicology (13.1)].

Cardiac Electrophysiology

At a dose five times the maximum recommended dose, dexlansoprazole does not prolong the QT interval to any clinically relevant extent.

12.3 Pharmacokinetics

The dual delayed-release formulation of DEXILANT results in a dexlansoprazole plasma concentration-time profile with two distinct peaks; the first peak occurs one to two hours after administration, followed by a second peak within four to five hours (see Figure 1). Dexlansoprazole is eliminated with a half-life of approximately one to two hours in healthy subjects and in patients with symptomatic GERD. No accumulation of dexlansoprazole occurs after multiple, once daily doses of DEXILANT 30 or 60 mg although mean AUCt and Cmax values of dexlansoprazole were slightly higher (less than 10%) on Day 5 than on Day 1.

Figure 1: Mean Plasma Dexlansoprazole Concentration – Time Profile Following Oral Administration of 30 or 60 mg DEXILANT Once Daily for 5 Days in Healthy Adult Subjects

The pharmacokinetics of dexlansoprazole are highly variable, with percent coefficient of variation (%CV) values for Cmax, AUC, and CL/F of greater than 30% (see Table 6).

Table 6. Mean (%CV) Pharmacokinetic Parameters for Adult Subjects on Day 5 After Administration of DEXILANT
Dose (mg) | Cmax (ng/mL) | AUC24 (ng∙h/mL) | CL/F (L/h)
30 | 658 (40%) (N=44) | 3,275 (47%) (N=43) | 11.4 (48%) (N=43)
60 | 1,397 (51%) (N=79) | 6,529 (60%) (N=73) | 11.6 (46%) (N=41)

Absorption

After oral administration of DEXILANT 30 or 60 mg to healthy subjects and symptomatic GERD patients, mean Cmax and AUC values of dexlansoprazole increased approximately dose proportionally (see Figure 1).

When granules of DEXILANT 60 mg are mixed with water and dosed via NG tube or orally via syringe, the bioavailability (Cmax and AUC) of dexlansoprazole was similar to that when DEXILANT 60 mg was administered as an intact capsule [see Dosage and Administration (2.3)].

Effect on Food

In food-effect studies in healthy subjects receiving DEXILANT under various fed conditions compared to fasting, increases in Cmax ranged from 12 to 55%, increases in AUC ranged from 9 to 37%, and Tmax varied (ranging from a decrease of 0.7 hours to an increase of three hours) [see Dosage and Administration (2.3)].

Distribution

Plasma protein binding of dexlansoprazole ranged from 96 to 99% in healthy subjects and was independent of concentration from 0.01 to 20 mcg/mL. The apparent volume of distribution (Vz/F) after multiple doses in symptomatic GERD patients was 40 L.

Elimination

Metabolism

Dexlansoprazole is extensively metabolized in the liver by oxidation, reduction, and subsequent formation of sulfate, glucuronide and glutathione conjugates to inactive metabolites. Oxidative metabolites are formed by the cytochrome P450 (CYP) enzyme system including hydroxylation mainly by CYP2C19, and oxidation to the sulfone by CYP3A4.

CYP2C19 is a polymorphic liver enzyme which exhibits three phenotypes in the metabolism of CYP2C19 substrates: extensive metabolizers (*1/*1), intermediate metabolizers (*1/mutant) and poor metabolizers (mutant/mutant). Dexlansoprazole is the major circulating component in plasma regardless of CYP2C19 metabolizer status. In CYP2C19 intermediate and extensive metabolizers, the major plasma metabolites are 5-hydroxy dexlansoprazole and its glucuronide conjugate, while in CYP2C19 poor metabolizers dexlansoprazole sulfone is the major plasma metabolite.

Excretion

Following the administration of DEXILANT, no unchanged dexlansoprazole is excreted in urine. Following the administration of [^14C] dexlansoprazole to six healthy male subjects, approximately 50.7% (standard deviation (SD): 9.0%) of the administered radioactivity was excreted in urine and 47.6% (SD: 7.3%) in the feces. Apparent clearance (CL/F) in healthy subjects was 11.4 to 11.6 L/hour, respectively, after five days of 30 or 60 mg once daily administration.

Specific Populations

Age: Pediatric Population

The pharmacokinetics of dexlansoprazole in patients under the age of 12 years have not been studied.

Patients 12 to 17 Years of Age

The pharmacokinetics of dexlansoprazole were studied in 36 patients 12 to 17 years of age with symptomatic GERD in a multicenter trial. Patients were randomized to receive DEXILANT 30 or 60 mg once daily for seven days. The dexlansoprazole mean Cmax and AUC in patients 12 to 17 years of age were 105 and 88%, respectively, compared to those observed in adults at the 30 mg dose, and were 81 and 78%, respectively, at the 60 mg dose (see Tables 6 and 7).

Table 7. Mean (%CV) Pharmacokinetic Parameters in Patients 12 to 17 Years of Age with Symptomatic GERD on Day 7 After Administration of DEXILANT Once Daily for 7 Days
Dose | Cmax (ng/mL) | AUCtau (ng∙h/mL) | CL/F (L/h)
30 mg (N=17) | 691 (53) | 2,886 (47) | 12.8 (48)
60 mg (N=18) | 1,136 (51) | 5,120 (58) | 15.3 (49)

Age: Geriatric Population The terminal elimination half-life of dexlansoprazole is significantly increased in geriatric subjects compared to younger subjects (2.2 and 1.5 hours, respectively). Dexlansoprazole exhibited higher systemic exposure (AUC) in geriatric subjects (34% higher) than younger subjects [see Use in Specific Populations (8.5)].

Sex

In a study of 12 male and 12 female healthy subjects who received a single dose of DEXILANT 60 mg, females had higher systemic exposure (AUC) (43% higher) than males. This difference in exposure between males and females does not represent a significant safety concern.

Renal Impairment

Dexlansoprazole is extensively metabolized in the liver to inactive metabolites, and no parent drug is recovered in the urine following an oral dose of dexlansoprazole. Therefore, the pharmacokinetics of dexlansoprazole are not expected to be altered in patients with renal impairment, and no studies were conducted in patients with renal impairment. In addition, the pharmacokinetics of lansoprazole were not clinically different in patients with mild, moderate or severe renal impairment compared to healthy subjects with normal renal function.

Hepatic Impairment

In a study of 12 patients with moderate hepatic impairment (Child-Pugh Class B) who received a single dose of 60 mg DEXILANT, the systemic exposure (AUC) of bound and unbound dexlansoprazole was approximately two times greater compared to subjects with normal hepatic function. This difference in exposure was not due to a difference in protein binding. No studies have been conducted in patients with severe hepatic impairment (Child-Pugh Class C) [see Dosage and Administration (2.2), Use in Specific Populations (8.6)].

Drug-Drug Interactions

Effect of Dexlansoprazole on Other Drugs

Cytochrome P 450 Interactions

Dexlansoprazole is metabolized, in part, by CYP2C19 and CYP3A4 [see Clinical Pharmacology (12.3)].

In vitro studies have shown that dexlansoprazole is not likely to inhibit CYP isoforms 1A1, 1A2, 2A6, 2B6, 2C8, 2C9, 2D6, 2E1, or 3A4. As such, no clinically relevant interactions with drugs metabolized by these CYP enzymes would be expected. Furthermore, in vivo studies showed that DEXILANT did not have an impact on the pharmacokinetics of coadministered phenytoin (CYP2C9 substrate) or theophylline (CYP1A2 substrate).

The subjects' CYP1A2 genotypes in the drug-drug interaction study with theophylline were not determined. Although in vitro studies indicated that DEXILANT has the potential to inhibit CYP2C19 in vivo, an in vivo drug- drug interaction study in mainly CYP2C19 extensive and intermediate metabolizers has shown that DEXILANT does not affect the pharmacokinetics of diazepam (CYP2C19 substrate).

Clopidogrel

Clopidogrel is metabolized to its active metabolite in part by CYP2C19. A study of healthy subjects who were CYP2C19 extensive metabolizers, receiving once daily administration of clopidogrel 75 mg alone or concomitantly with DEXILANT 60 mg (n=40), for nine days was conducted. The mean AUC of the active metabolite of clopidogrel was reduced by approximately 9% (mean AUC ratio was 91%, with 90% CI of 86 to 97%) when DEXILANT was coadministered compared to administration of clopidogrel alone. Pharmacodynamic parameters were also measured and demonstrated that the change in inhibition of platelet aggregation (induced by 5 mcM ADP) was related to the change in the exposure to clopidogrel active metabolite. The effect on exposure to the active metabolite of clopidogrel and on clopidogrel-induced platelet inhibition is not considered clinically important.

Effect of Other Drugs on Dexlansoprazole

Because dexlansoprazole is metabolized by CYP2C19 and CYP3A4, inducers and inhibitors of these enzymes may potentially alter exposure of dexlansoprazole.

12.5 Pharmacogenomics

Effect of CYP2C19 Polymorphism on Systemic Exposure of Dexlansoprazole

Systemic exposure of dexlansoprazole is generally higher in intermediate and poor metabolizers. In male Japanese subjects who received a single dose of DEXILANT 30 or 60 mg (N=2 to 6 subjects/group), mean dexlansoprazole Cmax and AUC values were up to two times higher in intermediate compared to extensive metabolizers; in poor metabolizers, mean Cmax was up to four times higher and mean AUC was up to 12 times higher compared to extensive metabolizers. Though such study was not conducted in Caucasians and African Americans, it is expected dexlansoprazole exposure in these races will be affected by CYP2C19 phenotypes as well.

13 NONCLINICAL TOXICOLOGY

13.1 Carcinogenesis, Mutagenesis, Impairment of Fertility

The carcinogenic potential of dexlansoprazole was assessed using lansoprazole studies. In two, 24 month carcinogenicity studies, Sprague-Dawley rats were treated orally with lansoprazole at doses of 5 to 150 mg/kg/day, about one to 40 times the exposure on a body surface (mg/m^2) basis of a 50 kg person of average height [1.46 m^2 body surface area (BSA)] given the recommended human dose of lansoprazole 30 mg/day.

Lansoprazole produced dose-related gastric ECL cell hyperplasia and ECL cell carcinoids in both male and female rats [see Clinical Pharmacology (12.2)].

In rats, lansoprazole also increased the incidence of intestinal metaplasia of the gastric epithelium in both sexes. In male rats, lansoprazole produced a dose-related increase of testicular interstitial cell adenomas. The incidence of these adenomas in rats receiving doses of 15 to 150 mg/kg/day (four to 40 times the recommended human lansoprazole dose based on BSA) exceeded the low background incidence (range = 1.4 to 10%) for this strain of rat.

In a 24 month carcinogenicity study, CD-1 mice were treated orally with lansoprazole doses of 15 to 600 mg/kg/day, two to 80 times the recommended human lansoprazole dose based on BSA. Lansoprazole produced a dose-related increased incidence of gastric ECL cell hyperplasia. It also produced an increased incidence of liver tumors (hepatocellular adenoma plus carcinoma). The tumor incidences in male mice treated with 300 and 600 mg lansoprazole/kg/day (40 to 80 times the recommended human lansoprazole dose based on BSA) and female mice treated with 150 to 600 mg lansoprazole/kg/day (20 to 80 times the recommended human lansoprazole dose based on BSA) exceeded the ranges of background incidences in historical controls for this strain of mice. Lansoprazole treatment produced adenoma of rete testis in male mice receiving 75 to 600 mg/kg/day (10 to 80 times the recommended human lansoprazole dose based on BSA).

A 26 week p53 (+/-) transgenic mouse carcinogenicity study of lansoprazole was not positive.

Lansoprazole was positive in the Ames test and the in vitro human lymphocyte chromosomal aberration assay. Lansoprazole was not genotoxic in the ex vivo rat hepatocyte unscheduled DNA synthesis (UDS) test, the in vivo mouse micronucleus test or the rat bone marrow cell chromosomal aberration test.

Dexlansoprazole was positive in the Ames test and in the in vitro chromosome aberration test using Chinese hamster lung cells. Dexlansoprazole was negative in the in vivo mouse micronucleus test.

The potential effects of dexlansoprazole on fertility and reproductive performance were assessed using lansoprazole studies. Lansoprazole at oral doses up to 150 mg/kg/day (40 times the recommended human lansoprazole dose based on BSA) was found to have no effect on fertility and reproductive performance of male and female rats.

14 CLINICAL STUDIES

14.1 Healing of Erosive Esophagitis in Adults

Two multicenter, double-blind, active-controlled, randomized, eight week studies were conducted in patients with endoscopically confirmed EE. Severity of the disease was classified based on the Los Angeles Classification Grading System (Grades A-D). Patients were randomized to one of the following three treatment groups: DEXILANT 60 mg once daily, DEXILANT 90 mg once daily or lansoprazole 30 mg once daily. Patients who were H. pylori positive or who had Barrett's Esophagus and/or definite dysplastic changes at baseline were excluded from these studies. A total of 4,092 patients were enrolled and ranged in age from 18 to 90 years (median age 48 years) with 54% male. Race was distributed as follows: 87% Caucasian, 5% Black and 8% Other. Based on the Los Angeles Classification, 71% of patients had mild EE (Grades A and B) and 29% of patients had moderate to severe EE (Grades C and D) before treatment.

The studies were designed to test noninferiority. If noninferiority was demonstrated then superiority would be tested. Although noninferiority was demonstrated in both studies, the finding of superiority in one study was not replicated in the other.

The proportion of patients with healed EE at Week 4 or 8 is presented below in Table 8.

Table 8. EE Healing Rates [Based on crude rate estimates, patients who did not have endoscopically documented healed EE and prematurely discontinued were considered not healed.] in Adults: All Grades
Study | Number of Patients (N) [Patients with at least one postbaseline endoscopy.] | Treatment Group (daily) | Week 4 % Healed | Week 8 [Primary efficacy endpoint.] % Healed | (95% CI) for the Treatment Difference (DEXILANT–Lansoprazole) by Week 8
1 | 657 | DEXILANT 60 mg | 70 | 87 | (-1.5, 6.1) [Demonstrated noninferiority to lansoprazole.]
1 | 648 | Lansoprazole 30 mg | 65 | 85 | (-1.5, 6.1) [Demonstrated noninferiority to lansoprazole.]
2 | 639 | DEXILANT 60 mg | 66 | 85 | (2.2, 10.5)
2 | 656 | Lansoprazole 30 mg | 65 | 79 | (2.2, 10.5)
CI = Confidence interval

DEXILANT 90 mg once daily was studied and did not provide additional clinical benefit over DEXILANT 60 mg once daily.

14.2 Maintenance of Healed Erosive Esophagitis and Relief of Heartburn in Adults

A multicenter, double-blind, placebo-controlled, randomized study was conducted in patients who successfully completed an EE study and showed endoscopically confirmed healed EE. Maintenance of healing and symptom resolution over a six month period was evaluated with DEXILANT 30 or 60 mg once daily compared to placebo. A total of 445 patients were enrolled and ranged in age from 18 to 85 years (median age 49 years), with 52% female. Race was distributed as follows: 90% Caucasian, 5% Black and 5% Other.

Sixty -six percent of patients treated with 30 mg of DEXILANT remained healed over the six month time period as confirmed by endoscopy (see Table 9).

Table 9. Maintenance Rates [Based on crude rate estimates, patients who did not have endoscopically documented relapse and prematurely discontinued were considered to have relapsed.] of Healed EE at Month 6 in Adults
Number of Patients (N) [Patients with at least one postbaseline endoscopy] | Treatment Group (daily) | Maintenance Rate (%)
125 | DEXILANT 30 mg | 66.4 [Statistically significant vs placebo]
119 | Placebo | 14.3

DEXILANT 60 mg once daily was studied and did not provide additional clinical benefit over DEXILANT 30 mg once daily.

The effect of DEXILANT 30 mg on maintenance of relief of heartburn was also evaluated. Upon entry into the maintenance study, a majority of patients' baseline heartburn severity was rated as none. DEXILANT 30 mg demonstrated a statistically significantly higher percent of 24 hour heartburn-free periods compared to placebo over the six month treatment period (see Table 10). The majority of patients treated with placebo discontinued due to relapse of EE between Month 2 and Month 6.

Table 10. Median Percentage of 24 Hour Heartburn-Free Periods of the Maintenance of Healed EE Study in Adults
 | Overall Treatment [Secondary efficacy endpoint] |  | Month 1 |  | Month 6
Treatment Group (daily) | N | Heartburn- Free 24 hour Periods (%) | N | Heartburn- Free 24 hour Periods (%) | N | Heartburn- Free 24 hour Periods (%)
DEXILANT 30 mg | 132 | 96.1 [Statistically significant vs placebo] | 126 | 96.7 | 80 | 98.3
Placebo | 141 | 28.6 | 117 | 28.6 | 23 | 73.3

14.3 Treatment of Symptomatic Non-Erosive GERD in Adults

A multicenter, double-blind, placebo-controlled, randomized, four week study was conducted in patients with a diagnosis of symptomatic non-erosive GERD made primarily by presentation of symptoms. These patients who identified heartburn as their primary symptom, had a history of heartburn for six months or longer, had heartburn on at least four of seven days immediately prior to randomization and had no esophageal erosions as confirmed by endoscopy. However, patients with symptoms which were not acid-related may not have been excluded using these inclusion criteria. Patients were randomized to one of the following treatment groups: DEXILANT 30 mg daily, 60 mg daily, or placebo. A total of 947 patients were enrolled and ranged in age from 18 to 86 years (median age 48 years) with 71% female. Race was distributed as follows: 82% Caucasian, 14% Black and 4% Other.

DEXILANT 30 mg provided statistically significantly greater percent of days with heartburn-free 24 hour periods over placebo as assessed by daily diary over four weeks (see Table 11). DEXILANT 60 mg once daily was studied and provided no additional clinical benefit over DEXILANT 30 mg once daily.

Table 11. Median Percentages of 24 Hour Heartburn-Free Periods During the 4 Week Treatment Period of the Symptomatic Non-Erosive GERD Study in Adults
N | Treatment Group (daily) | Heartburn-Free 24 hour Periods (%)
312 | DEXILANT 30 mg | 54.9 [Statistically significant vs placebo]
310 | Placebo | 18.5

A higher percentage of patients on DEXILANT 30 mg had heartburn-free 24 hour periods compared to placebo as early as the first three days of treatment and this was sustained throughout the treatment period (percentage of patients on Day 3: DEXILANT 38% vs placebo 15%; on Day 28: DEXILANT 63% vs placebo 40%).

14.4 Pediatric GERD

Use of DEXILANT in patients 12 to 17 years of age is supported by evidence from adequate and well- controlled studies of DEXILANT capsules in adults, with additional safety, efficacy, and pharmacokinetic data from studies performed in pediatric patients.

Healing of EE, Maintenance of Healed EE and Relief of Heartburn

In a multicenter, 36 week trial, 62 patients 12 to 17 years of age with a documented history of GERD for at least three months and endoscopically-proven erosive esophagitis (EE) were enrolled to evaluate the healing of EE, maintenance of healed EE and relief of heartburn, followed by an additional 12 weeks without treatment. The median age was 15 years, with males accounting for 61% of the patients. Based on the Los Angeles Classification Grading Scale, 97% of patients had mild EE (Grades A and B), and 3% of patients had moderate to severe EE (Grades C and D) before treatment.

In the first eight weeks, 62 patients were treated with DEXILANT 60 mg once daily to evaluate the healing of EE. Of the 62 patients, 58 patients completed the eight week trial, and 51 (88%) patients achieved healing of EE, as confirmed by endoscopy, over eight weeks of treatment (see Table 12).

Table 12. Healing of EE at Week 8 in Pediatric Patients 12 to 17 Years of Age
 | DEXILANT 60 mg
Proportion of randomized patients healed n (%) | 51/62 (82%)
95% CI | (70, 91) [Reported are the exact confidence limits.]
Proportion of evaluable patients healed [Includes only patients who underwent postbaseline endoscopy.] n (%) | 51/58 (88%)
95% CI | (77, 95)

After the initial eight weeks of treatment, all 51 patients with healed EE were randomized to receive treatment with DEXILANT 30 mg or placebo, once daily for an additional 16 weeks to evaluate maintenance of healing and symptom resolution. Maintenance of healing was assessed by endoscopy at Week 24. Of the 51 patients randomized, 13 patients discontinued early. Of these, five patients did not undergo postbaseline endoscopy. Eighteen of 22 (82%) evaluable patients treated with DEXILANT 30 mg remained healed over the 16 week treatment period as confirmed by endoscopy, compared with 14 of 24 (58%) in placebo (see Table 13).

Table 13. Maintenance of Healed EE at Week 24 [Following eight weeks of initial therapy and 16 weeks of maintenance therapy.] in Pediatric Patients 12 to 17 Years of Age
 | DEXILANT 30 mg | Placebo
Proportion of randomized patients who maintained healing of EE n (%) | 18/25 (72%) | 14/26 (54%)
95% Cl | (51, 88) [Reported are the exact confidence limits.] | (33, 73)
Proportion of evaluable patients who maintained healing of EE [Includes patients with at least one postbaseline endoscopy.] n (%) | 18/22 (82%) | 14/24 (58%)
95% Cl | (60, 95) | (37, 78)

Relief of heartburn was assessed in randomized patients during the 16 week maintenance period. The median percentage of 24 hour heartburn-free periods was 87% for those receiving DEXILANT 30 mg compared to 68% for those receiving placebo.

Out of the 32 patients who maintained healing of EE at the end of the 16 week maintenance period, 27 patients (16 treated with DEXILANT and 11 treated with placebo during the double-blind phase) were followed for an additional 12 weeks without therapy. Twenty -four of the 27 patients completed the 12 week follow-up period. One patient required treatment with acid suppression therapy.

Treatment of Symptomatic Non-Erosive GERD

In a single-arm, open-label, multicenter trial, 104 pediatric patients 12 to 17 years of age with symptomatic non-erosive GERD were treated with DEXILANT 30 mg once daily, for four weeks to evaluate safety and effectiveness. Patients had a documented history of GERD symptoms for at least three months prior to screening, reported heartburn on at least three out of seven days during screening, and had no esophageal erosions as confirmed by endoscopy. The median age was 15 years, with females accounting for 70% of the patients. During the four week treatment period, the median percentage of 24 hour heartburn free periods was 47%.

16 HOW SUPPLIED/STORAGE AND HANDLING

DEXILANT delayed-release capsules, 30 mg, are opaque, blue and gray with "TAP" and "30" imprinted on the capsule and supplied as:

NDC Number | Size
64764-171-11 | Unit dose package of 100
64764-171-30 | Bottle of 30
64764-171-90 | Bottle of 90
64764-171-19 | Bottle of 1000

DEXILANT delayed-release capsules, 60 mg, are opaque, blue with "TAP" and "60" imprinted on the capsule and supplied as:

NDC Number | Size
64764-175-11 | Unit dose package of 100
64764-175-30 | Bottle of 30
64764-175-90 | Bottle of 90
64764-175-19 | Bottle of 1000

STORAGE AND HANDLING

Store at 20 to 25°C (68 to 77°F); excursions permitted to 15 to 30°C (59 to 86°F) [see USP Controlled Room Temperature].

17 PATIENT COUNSELING INFORMATION

Advise the patient to read the FDA-approved patient labeling (Medication Guide and Instructions for Use).

Adverse Reactions

Advise patients to report to their healthcare provider if they experience any signs or symptoms consistent with:

- Hypersensitivity Reactions [see Contraindications (4)]
- Acute Tubulointerstitial Nephritis [see Warnings and Precautions (5.2)]
- Clostridium difficile-Associated Diarrhea [see Warnings and Precautions (5.3)]
- Bone Fracture [see Warnings and Precautions (5.4)]
- Severe Cutaneous Adverse Reactions [see Warnings and Precautions (5.5)]
- Cutaneous and Systemic Lupus Erythematosus [see Warnings and Precautions (5.6)]
- Cyanocobalamin (Vitamin B12) Deficiency [see Warnings and Precautions (5.7)]
- Hypomagnesemia and Mineral Metabolism [see Warnings and Precautions (5.8)]

Drug Interactions

Advise patients to report to their healthcare provider if they are taking rilpivirine-containing products [see Contraindications (4)] or high-dose methotrexate [see Warnings and Precautions (5.10)].

Pregnancy

Advise a pregnant woman of the potential risk to a fetus. Advise females of reproductive potential to inform their healthcare provider of a known or suspected pregnancy [see Use in Specific Populations (8.1)].

Administration

- Take without regard to food.
- Missed doses: If a dose is missed, administer as soon as possible. However, if the next scheduled dose is due, do not take the missed dose, and take the next dose on time. Do not take two doses at one time to make up for a missed dose.
- Swallow whole; do not chew.
- Can be opened and sprinkled on applesauce for patients who have trouble swallowing the capsule.
- Alternatively, the capsule can be administered with water via oral syringe or NG tube, as described in the Instructions for Use.

MEDICATION GUIDE
DEXILANT® (decks-i-launt) (dexlansoprazole)
delayed-release capsules, for oral use

Read this Medication Guide before you start taking DEXILANT and each time you get a refill. There may be new information. This information does not take the place of talking to your doctor about your medical condition or your treatment.

What is the most important information that I should know about DEXILANT?
DEXILANT may help your acid-related symptoms, but you could still have serious stomach problems. Talk with your doctor.
DEXILANT can cause serious side effects, including:

- A type of kidney problem (acute tubulointerstitial nephritis). Some people who take proton pump inhibitor (PPI) medicines, including DEXILANT, may develop a kidney problem called acute tubulointerstitial nephritis, that can happen at any time during treatment with PPI medicines. Call your doctor right away if you have a decrease in the amount that you urinate or if you have blood in your urine.
- Diarrhea. DEXILANT may increase your risk of getting severe diarrhea. This diarrhea may be caused by an infection (Clostridium difficile) in your intestines.
  Call your doctor right away if you have watery stool, stomach pain, and fever that does not go away.
- Bone fractures. People who take multiple daily doses of PPI medicines for a long period of time (a year or longer) may have an increased risk of fractures of the hip, wrist or spine. You should take DEXILANT exactly as prescribed, at the lowest dose possible for your treatment and for the shortest time needed. Talk to your doctor about your risk of bone fracture if you take DEXILANT.
- Certain types of lupus erythematosus. Lupus erythematosus is an autoimmune disorder (the body's immune cells attack other cells or organs in the body). Some people who take PPI medicines may develop certain types of lupus erythematosus or have worsening of the lupus they already have. Call your doctor right away if you have new or worsening joint pain or a rash on your cheeks or arms that gets worse in the sun.

DEXILANT can have other serious side effects. See "What are the possible side effects of DEXILANT?".

What is DEXILANT?
DEXILANT is a prescription medicine called a proton pump inhibitor (PPI). DEXILANT reduces the amount of acid in your stomach.
DEXILANT is used in people 12 years of age and older:

- for up to 8 weeks to heal acid-related damage to the lining of the esophagus (called erosive esophagitis or EE)
- for up to 6 months in adults and up to 16 weeks in children 12 to 17 years of age to continue healing of erosive esophagitis and relief of heartburn
- for 4 weeks to treat heartburn related to gastroesophageal reflux disease (GERD)

GERD happens when acid from your stomach enters the tube (esophagus) that connects your mouth to your stomach. This may cause a burning feeling in your chest or throat, sour taste or burping.
It is not known if DEXILANT is safe and effective in children under 12 years of age. DEXILANT is not recommended in children under 2 years of age and may harm them.
DEXILANT is not effective for symptoms of GERD in children under 1 year of age.

Who should not take DEXILANT? Do not take DEXILANT if you:

- are allergic to dexlansoprazole or any of the other ingredients in DEXILANT. See the end of this Medication Guide for a complete list of ingredients in DEXILANT.
- are taking a medicine that contains rilpivirine (EDURANT, COMPLERA, JULUCA) used to treat HIV-1 (Human Immunodeficiency Virus)

What should I tell my doctor before taking DEXILANT?
Before you take DEXILANT, tell your doctor about all of your medical conditions, including if you:

- have been told that you have low magnesium, calcium, potassium or sodium levels in your blood or you are taking a diuretic.
- have liver problems.
- are pregnant, think you may be pregnant or plan to become pregnant. DEXILANT may harm your unborn baby. Talk to your doctor about the possible risks to an unborn baby if DEXILANT is taken during pregnancy.
- are breastfeeding or plan to breastfeed. It is not known if DEXILANT passes into your breast milk or if it will affect your baby or your breast milk. Talk to your doctor about the best way to feed your baby if you take DEXILANT.

Tell your doctor about all the medicines you take, including prescription and over-the-counter medicines, vitamins, and herbal supplements. Keep a list of them to show your doctor and pharmacist when you get a new medicine.
DEXILANT may affect how other medicines work, and other medicines may affect how DEXILANT works. Especially tell your doctor if you take methotrexate (Otrexup, Rasuvo, Trexall, Reditrex, Xatmep) or digoxin. Know the medicines that you take.

How should I take DEXILANT?

- Take DEXILANT exactly as prescribed by your doctor.
- Do not change your dose or stop taking DEXILANT without talking to your doctor first.
- Take DEXILANT with or without food.
- Swallow DEXILANT whole. Do not chew the capsules or the granules that are in the capsules.
- If you have trouble swallowing a whole capsule, you can open the capsule and take the contents in applesauce. See the "Instructions for Use" at the end of this Medication Guide for instructions on how to take DEXILANT with applesauce.
- See the "Instructions for Use" at the end of this Medication Guide for instructions on how to mix and give DEXILANT with water using an oral syringe or through a nasogastric tube.
- If you miss a dose of DEXILANT, take it as soon as you remember. If it is almost time for your next dose, do not take the missed dose. Take your next dose at your regular time. Do not take 2 doses at the same time to make up for the missed dose.
- If you take too much DEXILANT, call your doctor or your poison control center at 1-800-222-1222 right away or go to the nearest hospital emergency room.

What are the possible side effects of DEXILANT?
DEXILANT may cause serious side effects, including:

- See "What is the most important information I should know about DEXILANT?".
- Vitamin B12 deficiency. DEXILANT reduces the amount of acid in your stomach. Stomach acid is needed to absorb Vitamin B12 properly. Talk with your doctor about the possibility of Vitamin B12 deficiency if you have been on DEXILANT for a long time (more than 3 years).
- Low magnesium levels in your body can happen in people who have taken DEXILANT for at least 3 months.Tell your doctor right away if you have symptoms of low magnesium levels, including seizures, dizziness, irregular heartbeat, jitteriness, muscle aches or weakness, and spasms of hands, feet or voice.
- Stomach growths (fundic gland polyps). People who take PPI medicines for a long time have an increased risk of developing a certain type of stomach growth called fundic gland polyps, especially after taking PPI medicines for more than 1 year.
- Severe skin reactions. DEXILANT can cause rare but severe skin reactions that may affect any part of your body. These serious skin reactions may need to be treated in a hospital and may be life threatening:
  - Skin rash which may have blistering, peeling or bleeding on any part of your skin (including your lips, eyes, mouth, nose, genitals, hands or feet).
  - You may also have fever, chills, body aches, shortness of breath, or enlarged lymph nodes.
  Stop taking DEXILANT and call your doctor right away. These symptoms may be the first sign of a severe skin reaction.

The most common side effects of DEXILANT in adults include:

- diarrhea
- stomach pain
- nausea
- common cold
- vomiting
- gas

The most common side effects of DEXILANT in children 12 to 17 years of age include:

- headache
- stomach pain
- diarrhea
- pain or swelling (inflammation) in your mouth, nose or throat

Other side effects:
Serious allergic reactions. Tell your doctor if you get any of the following symptoms with DEXILANT:

- rash
- face swelling
- throat tightness
- difficulty breathing

Your doctor may stop DEXILANT if these symptoms happen.
Tell your doctor if you have any side effect that bothers you or that does not go away.
These are not all the possible side effects of DEXILANT. For more information, ask your doctor or pharmacist. Call your doctor for medical advice about side effects. You may report side effects to FDA at 1-800-FDA-1088.

How should I store DEXILANT?

- Store DEXILANT at room temperature between 68°F to 77°F (20°C to 25°C).

Keep DEXILANT and all medicines out of the reach of children.

General information about the safe and effective use of DEXILANT.
Medicines are sometimes prescribed for purposes other than those listed in a Medication Guide. Do not use DEXILANT for a condition for which it was not prescribed. Do not give DEXILANT to other people, even if they have the same symptoms you have. It may harm them.
This Medication Guide summarizes the most important information about DEXILANT. If you would like more information, talk with your doctor. You can ask your doctor or pharmacist for information about DEXILANT that is written for health professionals.
For more information, go to www.DEXILANT.com or call 1-877-TAKEDA-7 (1-877-825-3327).

What are the ingredients in DEXILANT?
Active ingredient: dexlansoprazole.
Inactive ingredients: sugar spheres, magnesium carbonate, sucrose, low-substituted hydroxypropyl cellulose, titanium dioxide, hydroxypropyl cellulose, hypromellose 2910, talc, methacrylic acid copolymers, polyethylene glycol 8000, triethyl citrate, polysorbate 80, and colloidal silicon dioxide. The capsule shell is made of hypromellose, carrageenan and potassium chloride. Based on the capsule shell color, blue contains FD&C Blue No. 2 (or FD&C Blue No. 2 aluminum lake); gray contains black ferric oxide; and both contain titanium dioxide.
Distributed by:
Takeda Pharmaceuticals America, Inc.
Cambridge, MA 02142
DEXILANT and are registered trademarks of Takeda Pharmaceuticals U.S.A., Inc.
© 2025 Takeda Pharmaceuticals America, Inc. All rights reserved.

This Medication Guide has been approved by the U.S. Food and Drug Administration. Revised: 2/2025

INSTRUCTIONS FOR USE

DEXILANT® (decks-i-launt)
(dexlansoprazole)
delayed-release capsules, for oral use

Taking DEXILANT with applesauce:

1. Place 1 tablespoon of applesauce into a clean container.
2. Carefully open the capsule and sprinkle the granules onto the applesauce.
3. Swallow the applesauce and granules right away. Do not chew the granules. Do not save the applesauce and granules for later use.

Giving DEXILANT with water using an oral syringe:

1. Place 20 mL of water into a clean container.
2. Carefully open the capsule and empty the granules into the container of water.
3. Use an oral syringe to draw up the water and granule mixture.
4. Gently swirl the oral syringe to keep the granules from settling.
5. Place the tip of the oral syringe in your mouth. Give the medicine right away. Do not save the water and granule mixture for later use.
6. Refill the syringe with 10 mL of water and swirl gently. Place the tip of the oral syringe in your mouth and give the medicine that is left in the syringe.
7. Repeat step 6.

Giving DEXILANT with water through a nasogastric tube (NG tube):

For people who have an NG tube that is size 16 French or larger, DEXILANT may be given as follows:

1. Place 20 mL of water into a clean container.
2. Carefully open the capsule and empty the granules into the container of water.
3. Use a 60 mL catheter-tip syringe to draw up the water and granule mixture.
4. Gently swirl the catheter-tip syringe to keep the granules from settling.
5. Connect the catheter-tip syringe to the NG tube.
6. Give the mixture right away through the NG tube that goes into the stomach. Do not save the water and granule mixture for later use.
7. Refill the catheter-tip syringe with 10 mL of water and swirl gently. Flush the NG tube with the water.
8. Repeat step 7.

How should I store DEXILANT?

- Store DEXILANT at room temperature between 68°F to 77°F (20°C to 25°C).

Keep DEXILANT and all medicines out of the reach of children.

This Instructions for Use has been approved by the U.S. Food and Drug Administration.

Distributed by:
Takeda Pharmaceuticals America, Inc.
Cambridge, MA 02142

DEXILANT and are registered trademarks of Takeda Pharmaceuticals U.S.A., Inc.

© 2025 Takeda Pharmaceuticals America, Inc. All rights reserved.

Revised: February 2025

DEX006 R37

PRINCIPAL DISPLAY PANEL - 30 mg Capsule Bottle Label

NDC 64764-171-30

Rx only
30 Capsules

DEXILANT®
dexlansoprazole
delayed release
capsules

Dispense the
accompanying
Medication Guide
to each patient.

30 mg

PRINCIPAL DISPLAY PANEL - 60 mg Capsule Bottle Label

NDC 64764-175-30

Rx only
30 Capsules

DEXILANT®
dexlansoprazole
delayed release
capsules

Dispense the
accompanying
Medication Guide
to each patient.

60 mg